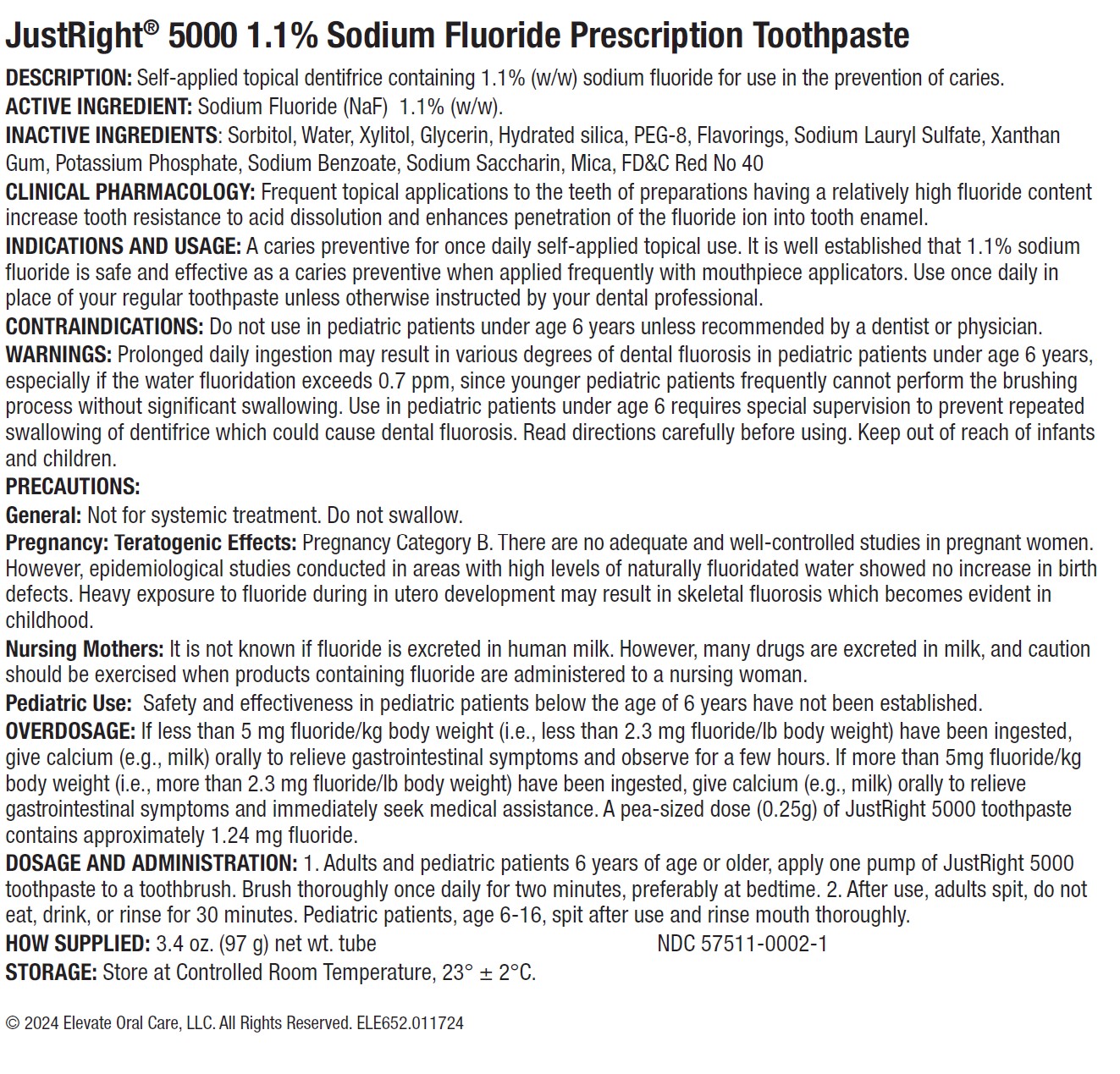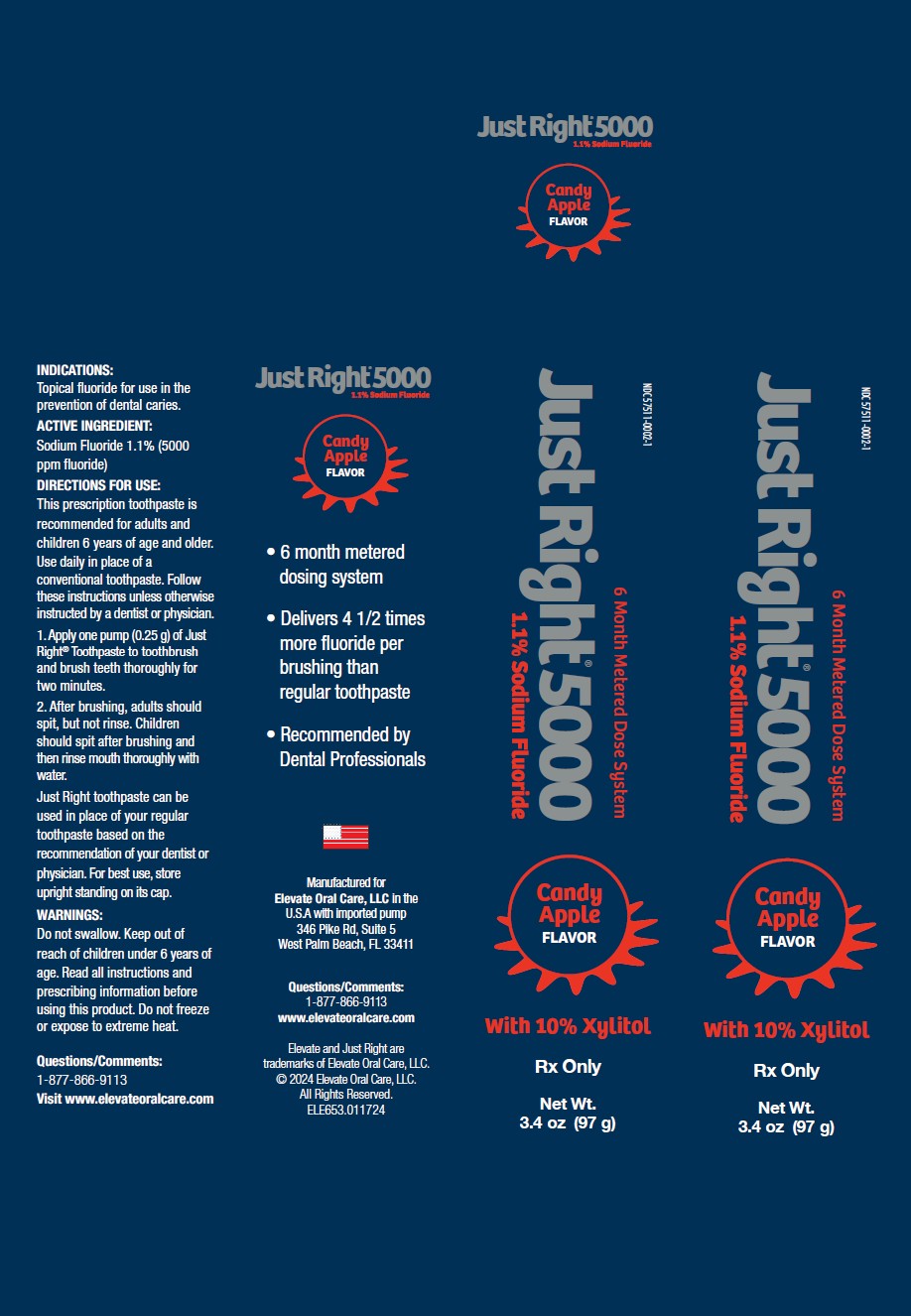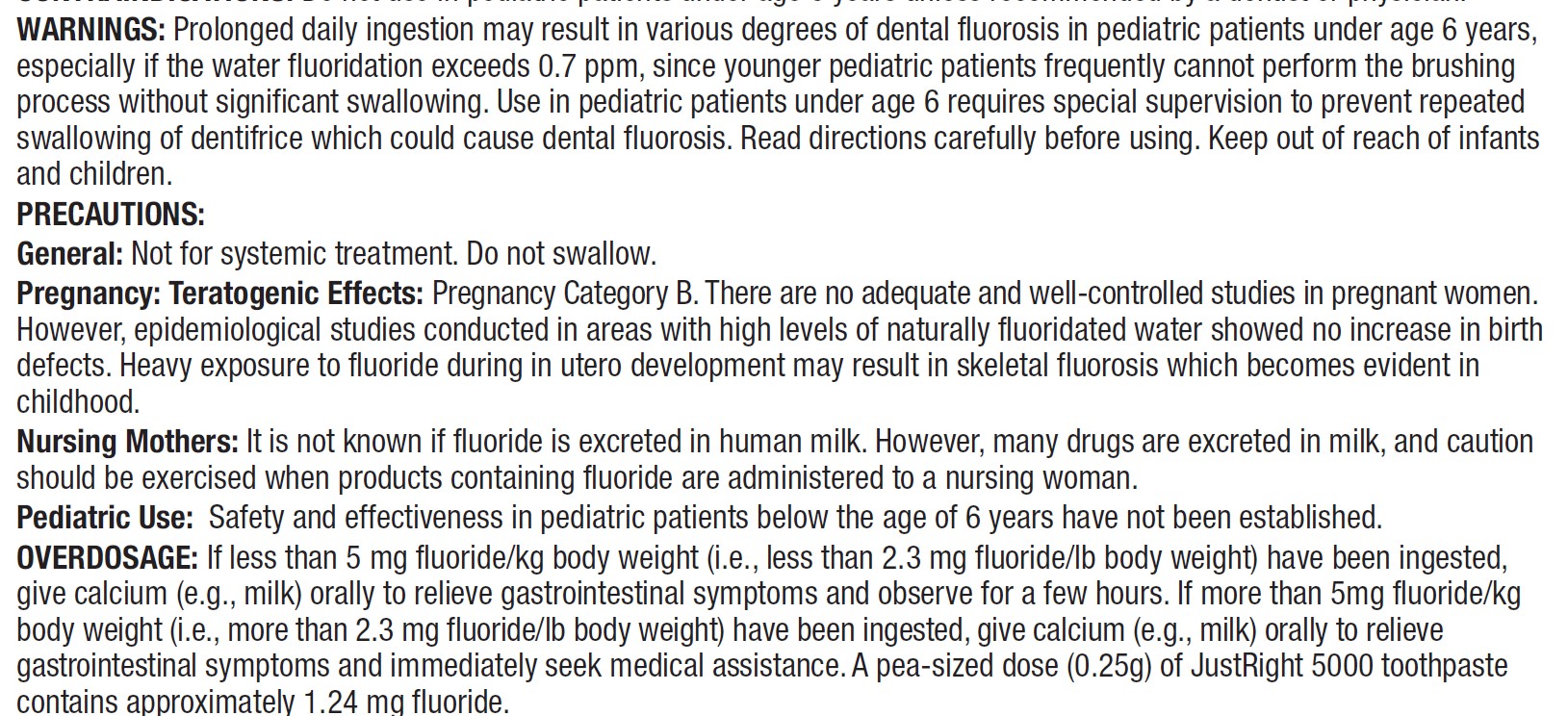 DRUG LABEL: Just Right 5000
NDC: 57511-0002 | Form: GEL, DENTIFRICE
Manufacturer: Elevate Oral Care
Category: prescription | Type: HUMAN PRESCRIPTION DRUG LABEL
Date: 20250919

ACTIVE INGREDIENTS: SODIUM FLUORIDE 1.1 g/100 g

Just Right 5000 Candy Apple